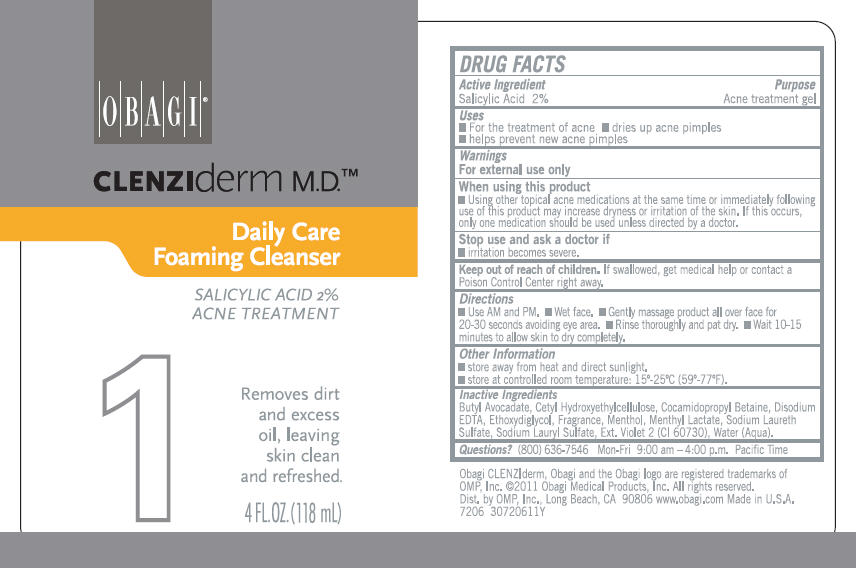 DRUG LABEL: CLENZIDERM DAILY CARE FOAMING CLEANSER 
NDC: 62032-111 | Form: LIQUID
Manufacturer: OMP, INC.
Category: otc | Type: HUMAN OTC DRUG LABEL
Date: 20111215

ACTIVE INGREDIENTS: SALICYLIC ACID 20 mg/1 mL
INACTIVE INGREDIENTS: SODIUM LAURETH SULFATE; DIETHYLENE GLYCOL MONOETHYL ETHER; SODIUM LAURYL SULFATE; COCAMIDOPROPYL BETAINE; CETYL HYDROXYETHYLCELLULOSE (350000 MW); EDETATE DISODIUM; MENTHOL; MENTHYL LACTATE; EXT. D&C VIOLET NO. 2; WATER

CLENZIDERM
DAILY CARE
FOAMING CLEANSER

DRUG FACTS

Active Ingredient

Salicylic Acid 2%

Purpose

Acne treatment gel

Uses

- For the treatment of acne
- dries up acne pimples
- helps prevent new acne pimples

Warnings

For external use only

When using this product

- Using other topical acne medications at the same time or immediately following use of this product may increase dryness or irritation of the skin. If this occurs, only one medication should be used unless directed by a doctor.

Stop use and ask a doctor if

- irritation becomes severe.

Keep out of reach of children. If swallowed, get medical help or contact a Poison Control Center right away.

Directions

- Use AM and PM.
- Wet face.
- Gently massage product all over face for 20-30 seconds avoiding eye area.
- Rinse thoroughly and pat dry.
- Wait 10-15 minutes to allow skin to dry completely.

Other Information

- store away from heat and direct sunlight.
- store at controlled room temperature: 15°-25°C (59°-77°F).

Inactive Ingredients

Butyl Avocadate, Cetyl Hydroxyethylcellulose, Cocamidopropyl Betaine, Disodium EDTA, Ethoxydiglycol, Fragrance, Menthol, Menthyl Lactate, Sodium Laureth Sulfate, Sodium Lauryl Sulfate, Ext. Violet 2 (CI 60730), Water (Aqua).

Questions?

(800) 636-7546 Mon-Fri 9:00 am – 4:00 p.m. Pacific Time

Dist. by OMP, Inc., Long Beach, CA 90806

PRINCIPAL DISPLAY PANEL - 118 mL Bottle Label

OBAGI®

CLENZIderm M.D.™

Daily Care
Foaming Cleanser

SALICYLIC ACID 2%
ACNE TREATMENT

1

Removes dirt
and excess
oil, leaving
skin clean
and refreshed.

4 FL.OZ. (118 mL)